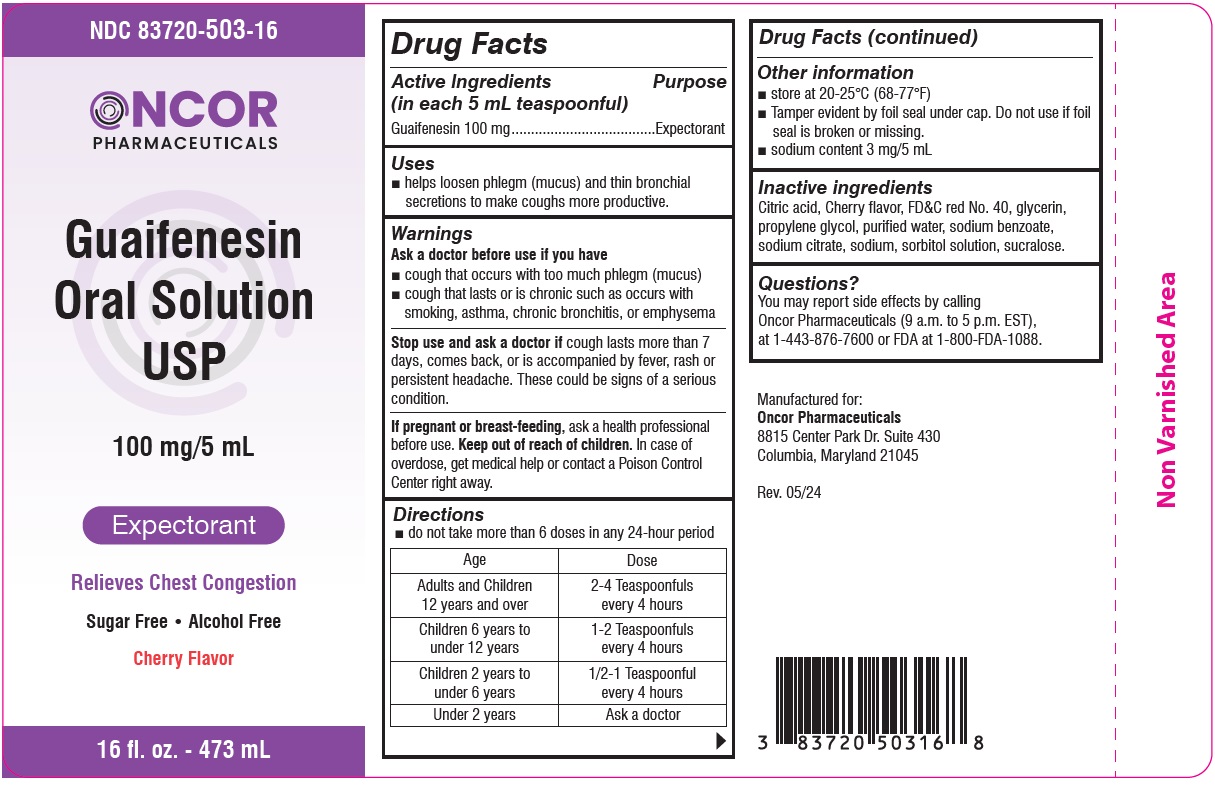 DRUG LABEL: Guaifenesin
NDC: 83720-503 | Form: LIQUID
Manufacturer: Oncor Pharmaceuticals
Category: otc | Type: HUMAN OTC DRUG LABEL
Date: 20260105

ACTIVE INGREDIENTS: GUAIFENESIN 100 mg/5 mL
INACTIVE INGREDIENTS: FD&C RED NO. 40; GLYCERIN; PROPYLENE GLYCOL; WATER; SODIUM BENZOATE; SODIUM CITRATE; SODIUM; SORBITOL SOLUTION; SUCRALOSE; CITRIC ACID MONOHYDRATE

Guaifenesin Oral Solution USP

Active ingredient (in each 5 mL teaspoonful)

Guaifenesin 100 mg

Purpose

Expectorant

Uses

- helps loosen phlegm (mucus) and thin bronchial secretions to make coughs more productive.

Warnings

Ask a doctor before use if you have

- cough that occurs with too much phlegm (mucus)
- cough that lasts or is chronic such as occurs with smoking, asthma, chronic bronchitis, or emphysema

Stop use and ask a doctor if

cough lasts more than 7 days, comes back, or is accompanied by fever, rash, or persistent headache. These could be signs of a serious condition.

If pregnant or breast-feeding,

ask a health professional before use.

Keep out of reach of children.

In case of overdose, get medical help or contact a Poison Control Center right away.

Directions

- do not take more than 6 doses in any 24-hour period
  Age | Dose
  Adults and Children 12 years and over | 2-4 Teaspoonfuls every 4 hours
  Children 6 years to under 12 years | 1-2 Teaspoonfuls every 4 hours
  Children 2 years to under 6 years | 1/2-1 Teaspoonful every 4 hours
  Under 2 years | Ask a doctor

Drug Facts(continued)

Other information

- store at 20°-25°C (68°-77°F)
- Tamper evident by foil seal under cap. Do not use if foil seal is broken or missing.
- sodium content 3 mg/5 mL

Inactive ingredients

Citric acid, Cherry flavor, FD&C red No. 40, glycerin, propylene glycol, purified water, sodium benzoate, sodium citrate, sodium, sorbitol solution, sucralose.

Questions?

You may report side effects by calling Oncor Pharmaceuticals (9 a.m. to 5 p.m. EST), at 1-443-876-7600 or FDA at 1-800-FDA-1088.

Manufactured for:
Oncor Pharmaceuticals
8815 Center Park Dr. Suite 430
Columbia, Maryland 21045

PRINCIPAL DISPLAY PANEL

NDC 83720-503-16

ONCOR PHARMACEUTICALS
Guaifenesin
Oral Solution USP
100 mg/5 mL
Expectorant

Relieves Chest Congestion

Sugar Free • Alcohol Free

Cherry Flavor
16 fl. oz. - 473 mL